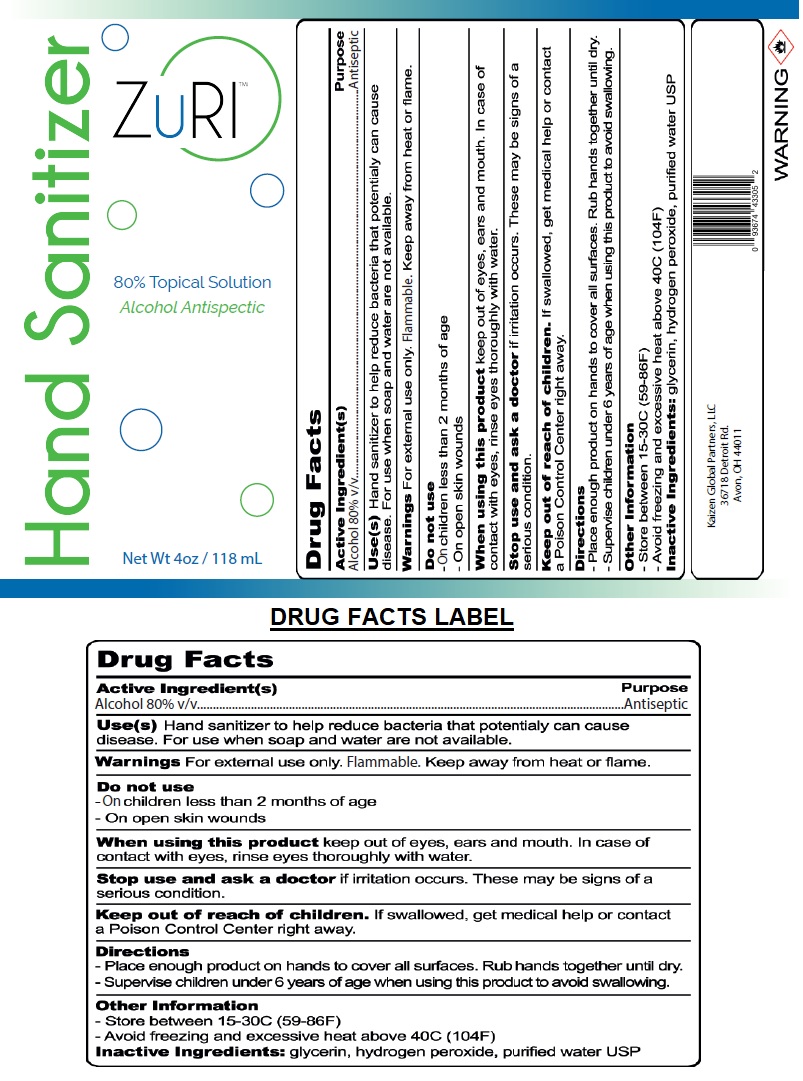 DRUG LABEL: ZuRI 80% Topical Solution Hand Sanitizer
NDC: 80347-080 | Form: LIQUID
Manufacturer: Kaizen Global Partners Llc
Category: otc | Type: HUMAN OTC DRUG LABEL
Date: 20200925

ACTIVE INGREDIENTS: ALCOHOL 80 mL/100 mL
INACTIVE INGREDIENTS: GLYCERIN; HYDROGEN PEROXIDE; WATER

ZuRI™ Hand Sanitizer

Active Ingredient(s)

Alcohol 80% v/v

Purpose

Antiseptic

INDICATIONS AND USAGE

Use(s) Hand Sanitizer to help reduce bacteria that potentially can cause disease. For use when soap and water are not available.

WARNINGS

Warnings For external use only. Flammable. Keep away from heat or flame.

Do not use

- On children less than 2 months of age.
- On open skin wounds

When using this product keep out of eyes, ears and mouth. In case of contact with eyes, rinse eyes thoroughly with water.

Stop use and ask a doctor if irritation occurs. These may be signs of a serious condition.

Keep out of reach of children. If swallowed, get medical help or contact a Poison Control Center right away.

Directions

- Place enough product on hand to cover all surfaces. Rub hands together until dry.

- Supervise children under 6 years of age when using this product to avoid swallowing.

Other Information

- Store between 15-30 C (59-86F)
- Avoid freezing and excessive heat above 40C (104F)

Inactive Ingredients: glycerin, hydrogen peroxide, purified water USP

80% Topical Solution

Alcohol Antiseptic

Kaizen Global Partners, LLC

36718 Detroid Rd.

Avon, OH 44011